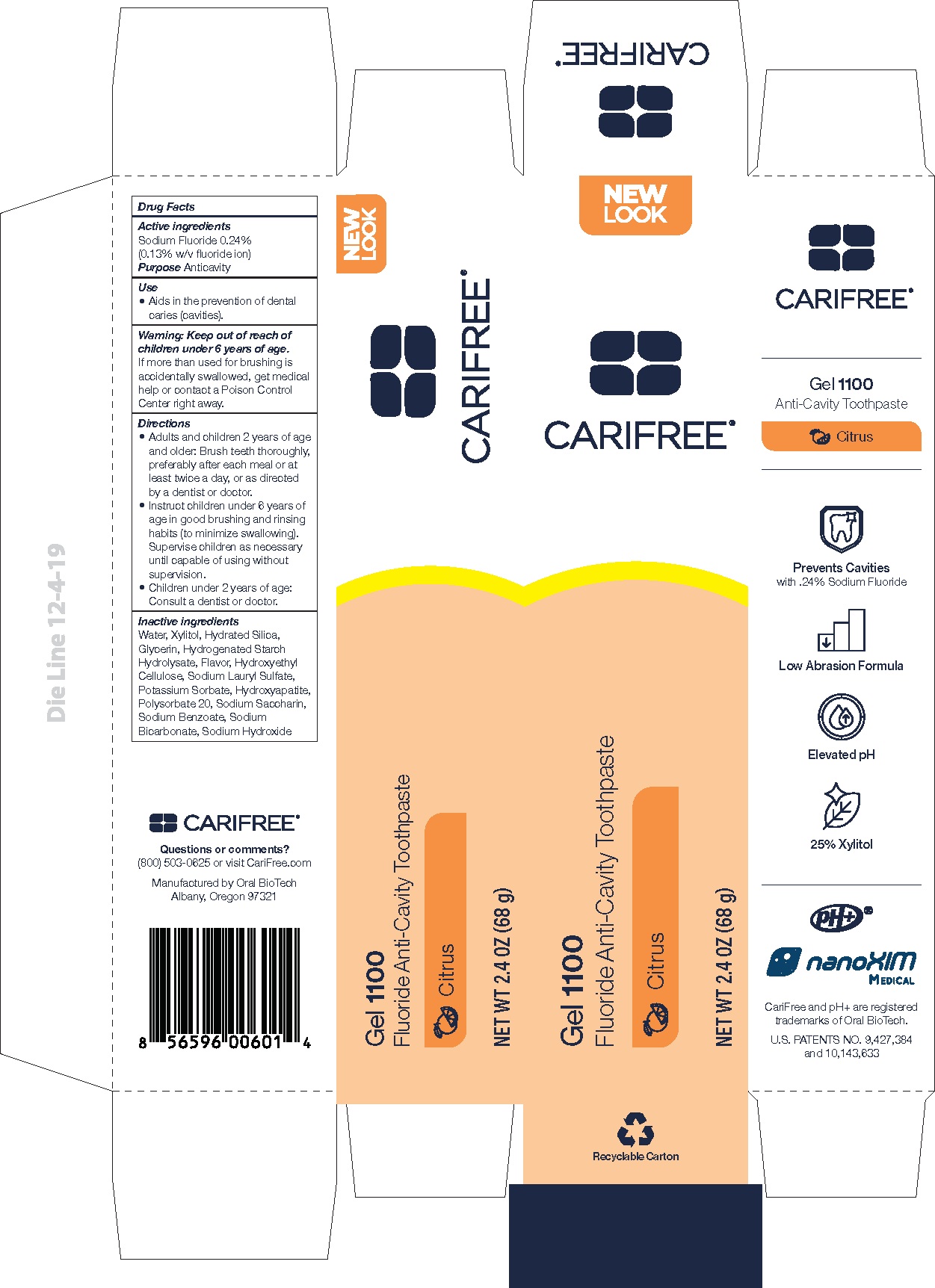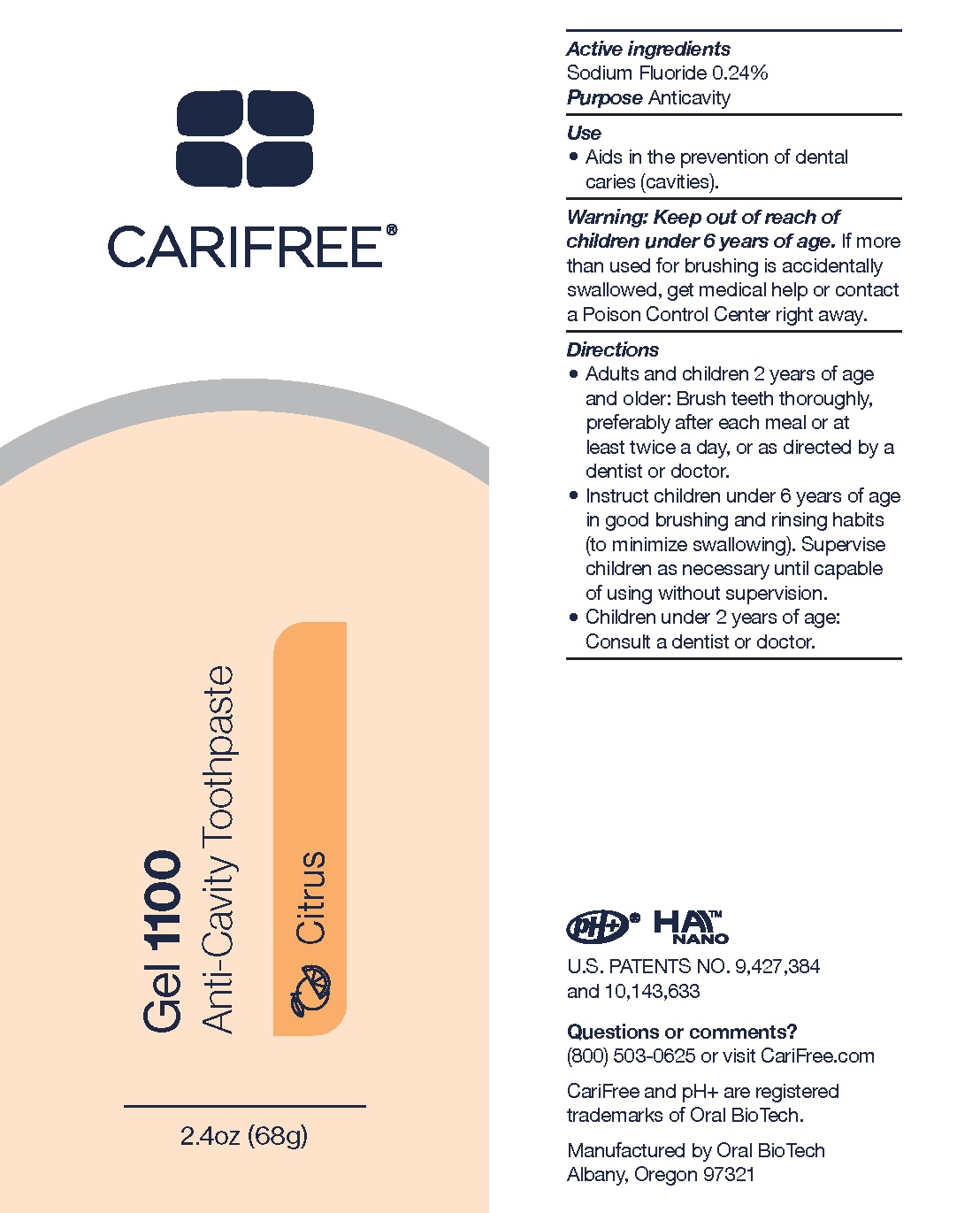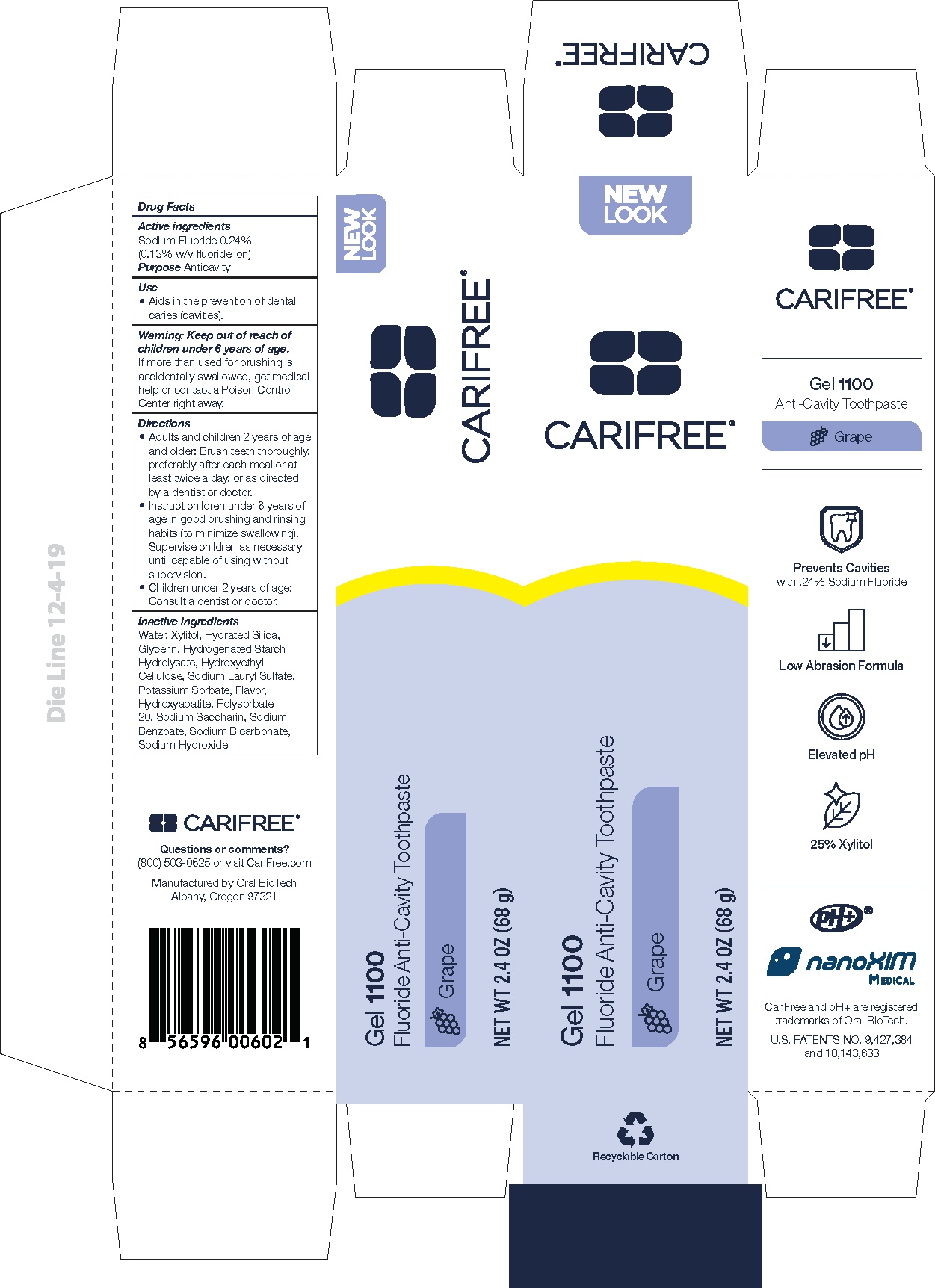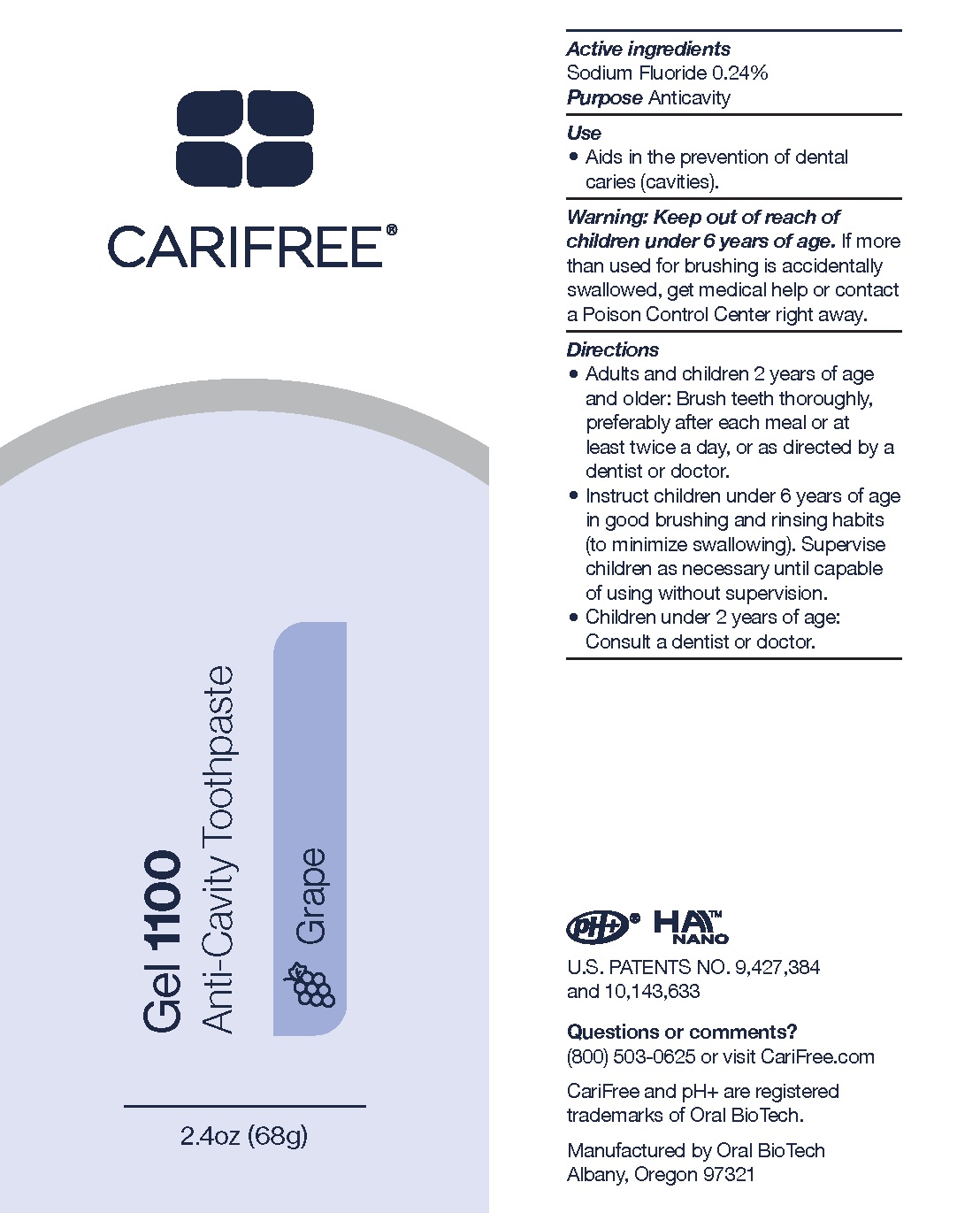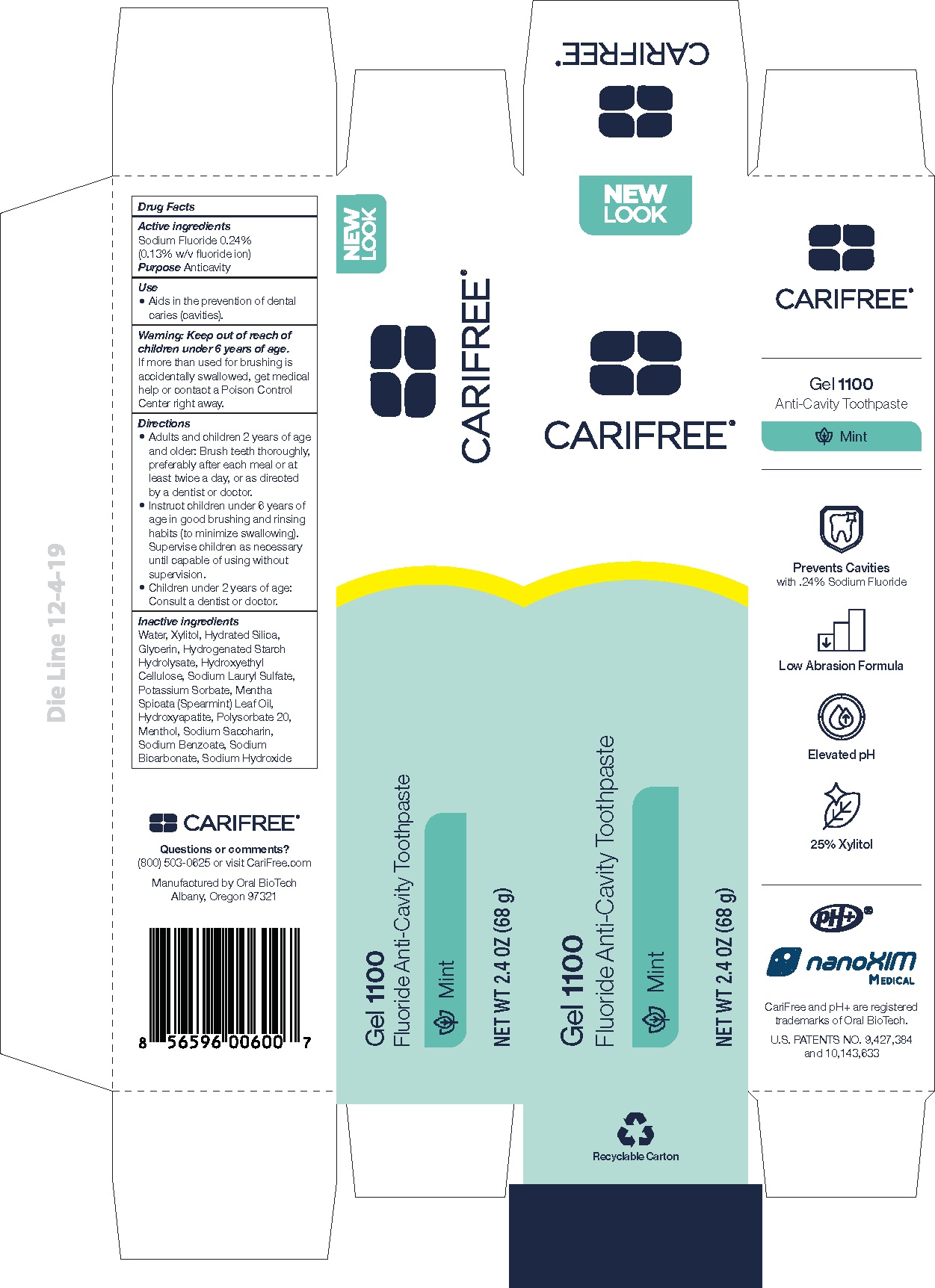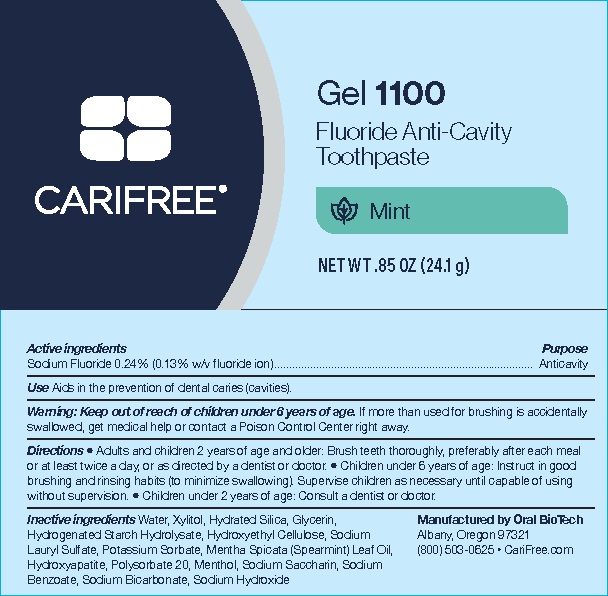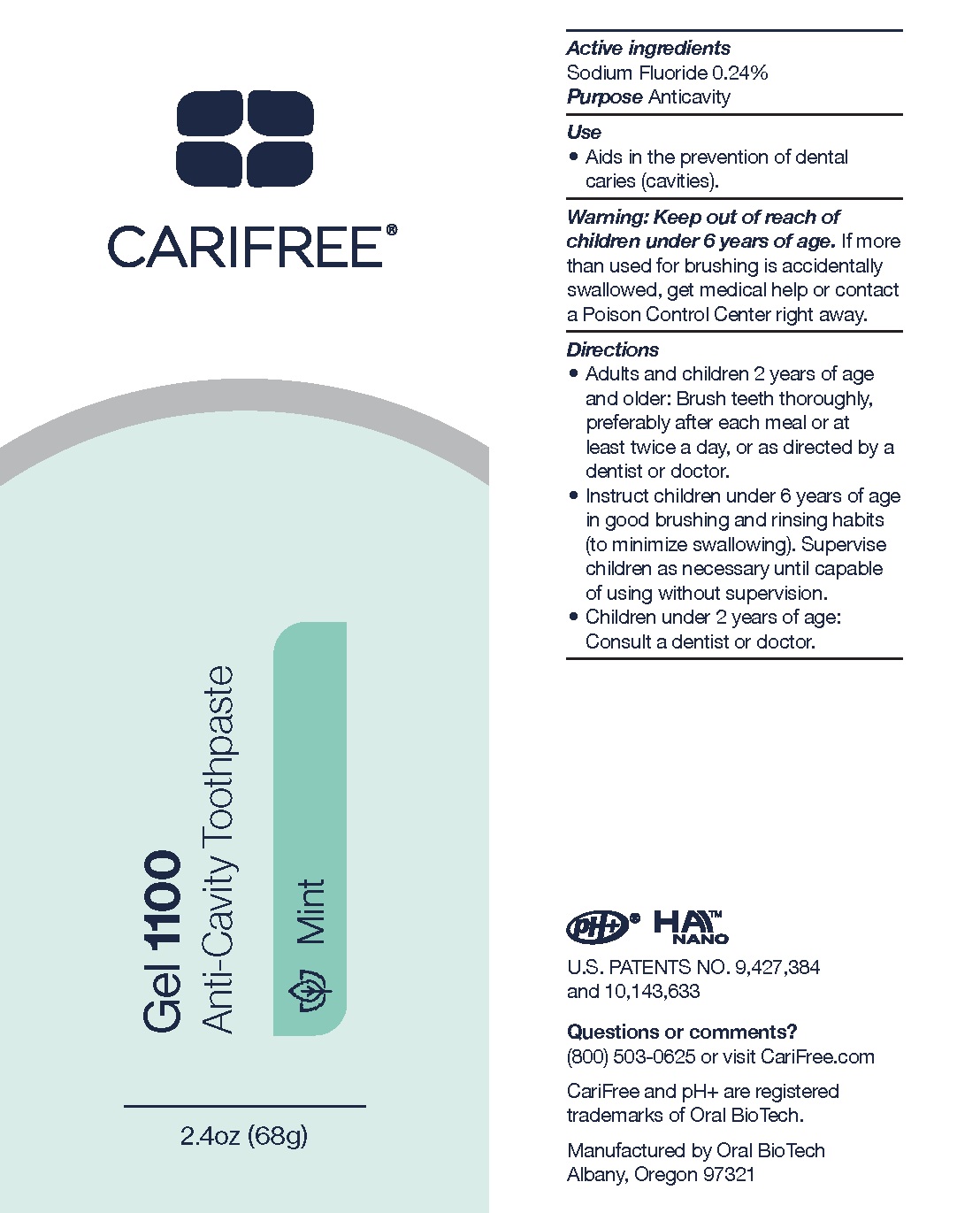 DRUG LABEL: Gel 1100
NDC: 61578-213 | Form: GEL, DENTIFRICE
Manufacturer: Dental Alliance Holdings LLC
Category: otc | Type: HUMAN OTC DRUG LABEL
Date: 20251229

ACTIVE INGREDIENTS: SODIUM FLUORIDE 1100 ug/1 g
INACTIVE INGREDIENTS: WATER; XYLITOL; HYDRATED SILICA; GLYCERIN; HYDROGENATED STARCH HYDROLYSATE; HYDROXYETHYL CELLULOSE (3000 CPS AT 1%); SODIUM LAURYL SULFATE; POTASSIUM SORBATE; MENTHA SPICATA OIL; HYDROXYAPATITE; POLYSORBATE 20; MENTHOL; SODIUM SACCHARIN; SODIUM BENZOATE; SODIUM BICARBONATE; SODIUM HYDROXIDE

Gel 1100

Active Ingredients

Sodium Fluoride 0.24% (0.13% w/v fluoride ion)

Purpose

Anticavity

Use

Aids in the prevention of dental caries (cavities).

Keep out of reach of children under 6 years of age.

If more than used for brushing is accidentally swallowed, get medical help or contact a Poison Control Center right away.

Directions

- Adults and children 6 years of age and older: Brush teeth thoroughly, preferably after each meal or at least twice a day, or as directed by a dentist or doctor.
- Instruct children under 6 years of age in good brushing and rinsing habits (to minimize swallowing). Supervise children as necessary until capable of using without supervision.
- Children under 2 years of age: Consult a dentist or doctor.

Inactive Ingredients

Water, Xylitol, Hydrated Silica, Glycerin, Hydrogenated Starch Hydrolysate, Hydroxyethyl Cellulose, Sodium Lauryl Sulfate, Potassium Sorbate, Mentha Spicata (Spearmint) Leaf Oil (Mint only), Flavor (Citrus and Grape only), Hydroxyapatite, Polysorbate 20, Menthol (Mint only), Sodium Saccharin, Sodium Benzoate, Sodium Bicarbonate, Sodium Hydroxide

CARIFREE Gel 1100 Anti-Cavity Toothpaste Mint 68 g - NDC 61578-213-01

CARIFREE®

Gel 1100

Anti-Cavity Toothpaste

Mint

2.4oz (68g)

Active ingredients

Sodium Fluoride 0.24%

Purpose Anticavity

Use

- Aids in the prevention of dental caries (cavities).

Warning: Keep out of reach of children under 6 years of age. If more than used for brushing is accidentally swallowed, get medical help or contact a Poison Control Center right away.

Directions

- Adults and children 6 years of age and older: Brush teeth thoroughly, preferably after each meal or at least twice a day, or as directed by a dentist or doctor.
- Instruct children under 6 years of age in good brushing and rinsing habits (to minimize swallowing). Supervise children as necessary until capable of using without supervision.
- Children under 2 years of age: Consult a dentist or doctor.

pH+® HAITM NANO

U.S. PATENTS NO. 9,427,384 and 10,143,633

Questions or comments?

(800) 503-0625 or visit CariFree.com

CariFree and pH+ are registered trademarks of Oral BioTech.

Manufactured by Oral BioTech

Albany, Oregon 97321

CARIFREE®

Gel 1100

Fluoride Anti-Cavity Toothpaste

Mint

NET WT 2.4 OZ (68 g)

Drug Facts

Active ingredients

Sodium Fluoride 0.24%

Purpose Anticavity

Use

- Aids in the prevention of dental caries (cavities).

Warning: Keep out of reach of children under 6 years of age

If more than used for brushing is accidentally swallowed, get medical help or contact a Poison Control Center right away.

Directions

- Adults and children 6 years of age and older: Brush teeth thoroughly, preferably after each meal or at least twice a day, or as directed by a dentist or doctor.
- Instruct children under 6 years of age in good brushing and rinsing habits (to minimize swallowing). Supervise children as necessary until capable of using without supervision.
- Children under 2 years of age: Consult a dentist or doctor.

Inactive ingredients

Water, Xylitol, Hydrated Silica, Glycerin, Hydrogenated Starch Hydrolysate, Hydroxyethyl Cellulose, Sodium Lauryl Sulfate, Potassium Sorbate, Mentha Spicata (Spearmint) Leaf Oil, Hydroxyapatite, Polysorbate 20, Menthol, Sodium Saccharin, Sodium Benzoate, Sodium Bicarbonate, Sodium Hydroxide

CARIFREE®

Questions or comments?

(800) 503-0625 or visit CariFree.com

CariFree and pH+ are registered trademarks of Oral BioTech.

Manufactured by Oral BioTech

Albany, Oregon 97321

Prevents Cavities

with .24% Sodium Fluoride

Low Abrasion Formula

Elevated pH

25% Xylitol

pH+®

nanoXIM Medical

CariFree and pH+ are registered trademarks of Oral BioTech.

U.S. PATENTS NO. 9,427,384 and 10,143,63

CARIFREE Gel 1100 Anti-Cavity Toothpaste Mint 24.1 g - NDC 61578-213-02

CARIFREE®

Gel 1100

Fluoride Anti-Cavity Toothpaste

Mint

NET WT .85 OZ (24.1 g)

Active ingredients | Purpose
Sodium Fluoride 0.24% (0.13 % w/v fluoride ion) | Anticavity

Use Aids in the prevention of dental caries (cavities).

Warning: Keep out of reach of children under 6 years of age If more than used for brushing is accidentally swallowed, get medical help or contact a Poison Control Center right away.

Directions • Adults and children 6 years of age and older: Brush teeth thoroughly, preferably after each meal or at least twice a day, or as directed by a dentist or doctor. • Children under 6 years of age: Instruct in good brushing and rinsing habits (to minimize swallowing). Supervise children as necessary until capable of using without supervision. • Children under 2 years of age: Consult a dentist or doctor.

Inactive ingredients Water, Xylitol, Hydrated Silica, Glycerin, Hydrogenated Starch Hydrolysate, Hydroxyethyl Cellulose, Sodium Lauryl Sulfate, Potassium Sorbate, Mentha Spicata (Spearmint) Leaf Oil, Hydroxyapatite, Polysorbate 20, Menthol, Sodium Saccharin, Sodium Benzoate, Sodium Bicarbonate, Sodium Hydroxide

Manufactured by Oral BioTech

Albany, Oregon 97321

(800) 503-0625 • CariFree.com

CARIFREE Gel 1100 Anti-Cavity Toothpaste Citrus 68 g - NDC 61578-214-01

CARIFREE®

Gel 1100

Anti-Cavity Toothpaste

Mint

2.4oz (68g)

Active ingredients

Sodium Fluoride 0.24%

Purpose Anticavity

Use

- Aids in the prevention of dental caries (cavities).

Warning: Keep out of reach of children under 6 years of age. If more than used for brushing is accidentally swallowed, get medical help or contact a Poison Control Center right away.

Directions

- Adults and children 6 years of age and older: Brush teeth thoroughly, preferably after each meal or at least twice a day, or as directed by a dentist or doctor.
- Instruct children under 6 years of age in good brushing and rinsing habits (to minimize swallowing). Supervise children as necessary until capable of using without supervision.
- Children under 2 years of age: Consult a dentist or doctor.

pH+® HAITM NANO

U.S. PATENTS NO. 9,427,384 and 10,143,633

Questions or comments?

(800) 503-0625 or visit CariFree.com

CariFree and pH+ are registered trademarks of Oral BioTech.

Manufactured by Oral BioTech

Albany, Oregon 97321

CARIFREE®

Gel 1100

Fluoride Anti-Cavity Toothpaste

Mint

NET WT 2.4 OZ (68 g)

Drug Facts

Active ingredients

Sodium Fluoride 0.24%

Purpose Anticavity

Use

- Aids in the prevention of dental caries (cavities).

Warning: Keep out of reach of children under 6 years of age

If more than used for brushing is accidentally swallowed, get medical help or contact a Poison Control Center right away.

Directions

- Adults and children 6 years of age and older: Brush teeth thoroughly, preferably after each meal or at least twice a day, or as directed by a dentist or doctor.
- Instruct children under 6 years of age in good brushing and rinsing habits (to minimize swallowing). Supervise children as necessary until capable of using without supervision.
- Children under 2 years of age: Consult a dentist or doctor.

Inactive ingredients

Water, Xylitol, Hydrated Silica, Glycerin, Hydrogenated Starch Hydrolysate, Flavor, Hydroxyethyl Cellulose, Sodium Lauryl Sulfate, Potassium Sorbate, Hydroxyapatite, Polysorbate 20, Sodium Saccharin, Sodium Benzoate, Sodium Bicarbonate, Sodium Hydroxide

CARIFREE®

Questions or comments?

(800) 503-0625 or visit CariFree.com

CariFree and pH+ are registered trademarks of Oral BioTech.

Manufactured by Oral BioTech

Albany, Oregon 97321

Prevents Cavities

with .24% Sodium Fluoride

Low Abrasion Formula

Elevated pH

25% Xylitol

pH+®

nanoXIM Medical

CariFree and pH+ are registered trademarks of Oral BioTech.

U.S. PATENTS NO. 9,427,384 and 10,143,63

CARIFREE Gel 1100 Anti-Cavity Toothpaste Grape 68 g - NDC 61578-217-01

CARIFREE®

Gel 1100

Anti-Cavity Toothpaste

Grape

2.4oz (68g)

Active ingredients

Sodium Fluoride 0.24%

Purpose Anticavity

Use

- Aids in the prevention of dental caries (cavities).

Warning: Keep out of reach of children under 6 years of age. If more than used for brushing is accidentally swallowed, get medical help or contact a Poison Control Center right away.

Directions

- Adults and children 6 years of age and older: Brush teeth thoroughly, preferably after each meal or at least twice a day, or as directed by a dentist or doctor.
- Instruct children under 6 years of age in good brushing and rinsing habits (to minimize swallowing). Supervise children as necessary until capable of using without supervision.
- Children under 2 years of age: Consult a dentist or doctor.

pH+® HAITM NANO

U.S. PATENTS NO. 9,427,384 and 10,143,633

Questions or comments?

(800) 503-0625 or visit CariFree.com

CariFree and pH+ are registered trademarks of Oral BioTech.

Manufactured by Oral BioTech

Albany, Oregon 97321

CARIFREE®

Gel 1100

Fluoride Anti-Cavity Toothpaste

Grape

NET WT 2.4 OZ (68 g)

Drug Facts

Active ingredients

Sodium Fluoride 0.24%

Purpose Anticavity

Use

- Aids in the prevention of dental caries (cavities).

Warning: Keep out of reach of children under 6 years of age

If more than used for brushing is accidentally swallowed, get medical help or contact a Poison Control Center right away.

Directions

- Adults and children 6 years of age and older: Brush teeth thoroughly, preferably after each meal or at least twice a day, or as directed by a dentist or doctor.
- Instruct children under 6 years of age in good brushing and rinsing habits (to minimize swallowing). Supervise children as necessary until capable of using without supervision.
- Children under 2 years of age: Consult a dentist or doctor.

Inactive ingredients

Water, Xylitol, Hydrated Silica, Glycerin, Hydrogenated Starch Hydrolysate, Hydroxyethyl Cellulose, Sodium Lauryl Sulfate, Potassium Sorbate, Flavor, Hydroxyapatite, Polysorbate 20, Sodium Saccharin, Sodium Benzoate, Sodium Bicarbonate, Sodium Hydroxide

CARIFREE®

Questions or comments?

(800) 503-0625 or visit CariFree.com

CariFree and pH+ are registered trademarks of Oral BioTech.

Manufactured by Oral BioTech

Albany, Oregon 97321

Prevents Cavities

with .24% Sodium Fluoride

Low Abrasion Formula

Elevated pH

25% Xylitol

pH+®

nanoXIM Medical

CariFree and pH+ are registered trademarks of Oral BioTech.

U.S. PATENTS NO. 9,427,384 and 10,143,63